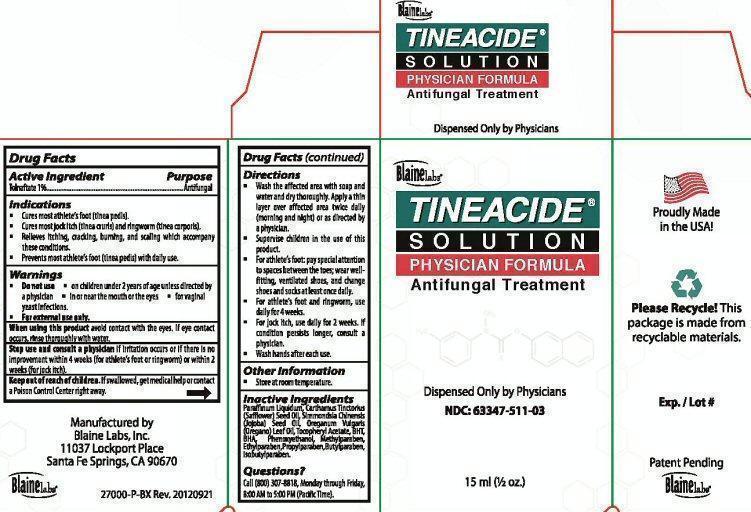 DRUG LABEL: TINEACIDE 
NDC: 63347-511 | Form: LIQUID
Manufacturer: Blaine Labs Inc.
Category: otc | Type: HUMAN OTC DRUG LABEL
Date: 20231221

ACTIVE INGREDIENTS: TOLNAFTATE 140 mg/15 mL
INACTIVE INGREDIENTS: MINERAL OIL; SAFFLOWER OIL; JOJOBA OIL; OREGANO LEAF OIL; .ALPHA.-TOCOPHEROL ACETATE; BUTYLATED HYDROXYTOLUENE; BUTYLATED HYDROXYANISOLE; PHENOXYETHANOL; METHYLPARABEN; ETHYLPARABEN; PROPYLPARABEN; ISOBUTYLPARABEN; BUTYLPARABEN

Active Ingredients

Drug facts

Active Ingredient

TOLNAFTATE 1%

Purpose

Antifungal

Keep out of reach of children. If swallowed, get medical help or contact a Poison control Center right away.

Indications

- Cures most athlete's foot (tinea pedis).
- Cures most jock itch (tinea cruris) and ring worm (tinea corporis).
- Relieves itching, cracking, burning, and scaling which accompany these conditions.
- Prevents most athlete's foot (tinea pedis) with daily use.

Warnings

- Do not use
- on children under 2 years of age unless directed by a physician
- in or near mouth or eyes
- for vaginal yeast infections
- For external use only

When using this product avoid contact with the eyes. If eye contact occurs, rinse thoroughly with water.

Stop Use And Consult A Physician

Stop use and ask a physician if irritation occurs or if there is no improvement within 4 weeks (for athlete's foot or ringworm) or within 2 weeks (for jock itch).

Directions

- Wash the affected ares with soap and water and dry thoroughly. Apply a thin layer over affected area twice daily (morning and night) or as directed by a physician.
- Supervise children in the use of this product.
- For athlete's foot pay special attention to spaces between the toes, wear well-fitting, ventilated shoes, and change shoes and socks at least once daily.
- For athlete's foot and ringworm, use daily for 4 weeks.
- For jock itch, use daily for 2 weeks. If condition persists longer, consult a physician.
- wash hands after each use.

Other Information

- Store at room temperature.

Questions?

Call (800)307-8818, Monday through Friday, 8:00 AM to 5:00 PM (Pacific Time).

Inactive Ingredients

Paraffnum Liquidum, Carthamus Tinctorius (Safflower) Seed Oil, Simmondsia Chinensis (Jojoba) Seed Oil, Oreganum Vulgaris (Oregano) Leaf Oil, Tocopheryl acetate, BHT, BHA, Phenoxyethanol, Methylparaben, Ethylparaben, Propylparaben, Butylparaben, Isobutylpapaben.

Package Label Tineacide Solution Physician Formula

Blaine Labs

TINEACIDE SOLUTION PHYSICIAN FORMULA

Antifungal Treatment

Dispensed Only by Physicians

NDC: 63347-511-03

15ml (1/2 oz.)

Proudly Made in the USA

Please Recycle! This package is made from recyclable materials.

Exp. / Lot #

Patent Pending

Blaine Labs

Manufactured by

Blaine Labs, Inc

11037 Lockport Place

Sante Fe Springs, CA 90670

27000-P-BX Rev. 20120921

res